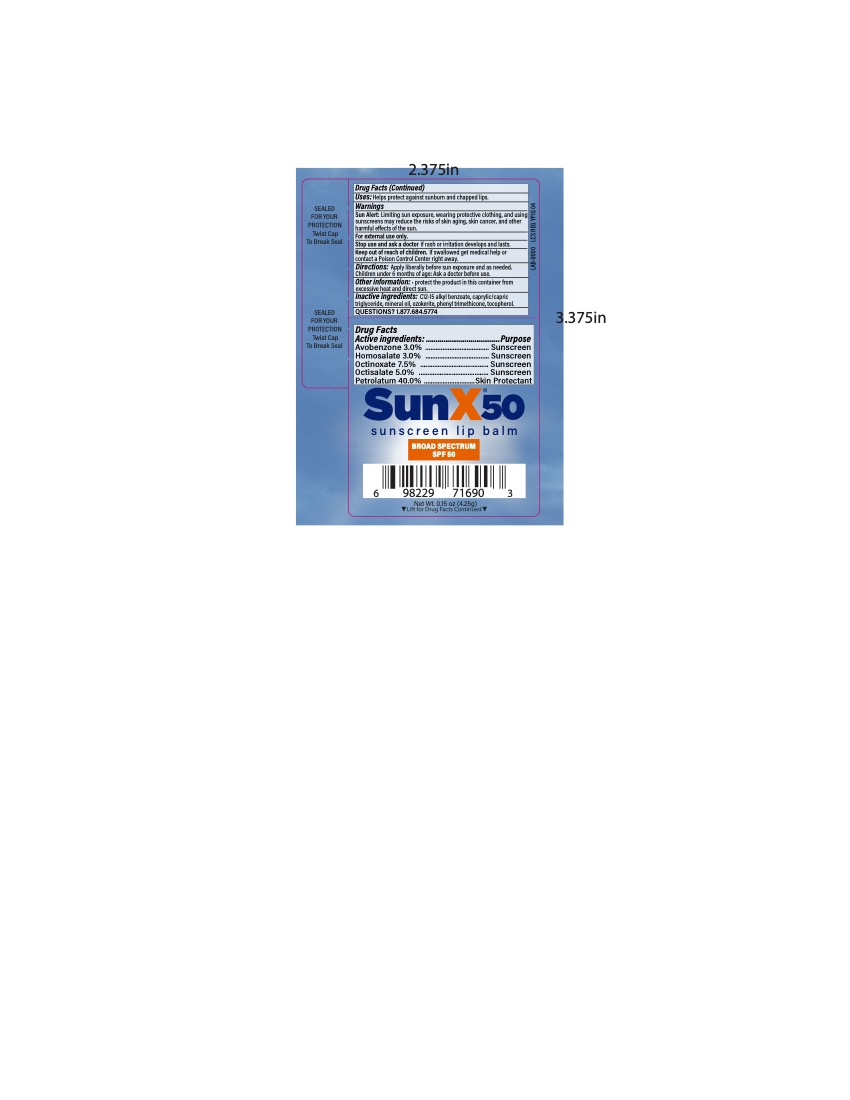 DRUG LABEL: Sun X SPF 50 Broad Spectrum Sunscreen Lip Balm
NDC: 65753-108 | Form: LIPSTICK
Manufacturer: CoreTex Products, INC
Category: otc | Type: HUMAN OTC DRUG LABEL
Date: 20231120

ACTIVE INGREDIENTS: PETROLATUM 40 g/100 mL; OCTISALATE 5 g/100 mL; OCTINOXATE 7.5 g/100 mL; AVOBENZONE 3 g/100 mL; HOMOSALATE 3 g/100 mL
INACTIVE INGREDIENTS: MINERAL OIL; WHITE WAX; ALKYL (C12-15) BENZOATE; COCONUT OIL; PHENYL TRIMETHICONE; TOCOPHEROL

Sun X 50 Lip Balm
65753-108

Active Ingredients:

Avobenzone…3.0%

Homosalate…3.0%

Octinoxate......7.5%

Octisalate…...5.0%

Petrolatum....40.0%

Purpose

Sunscreen

Sunscreen

Sunscreen

Sunscreen

Skin Protectant

Uses

Helps protect against sunburn and chapped lips.

Warnings

Sun Alert: Limiting sun exposure, wearing protective clothing, and using sunscreens may reduce the risks of skin aging , skin cancer, and other harmful effects of the sun.

Stop use and ask a doctor

if rash or irritation develops and lasts.

Keep out of reach of children.

If swallowed, get medical help or contact a Poison Control Center right away.

Directions:

Apply liberally before sun exposure and as needed.

Children under 6 months of age: Ask a doctor before use.

Other information:

protect the product in this container from excessive heat and direct sun.

Inactive Ingredients

C12-15 alkyl benzoate, caprylic/capric triglyceride, mineral oil, ozokerite, phenyl trimethicone, tocopherol

Questions?

1.877.684.5774